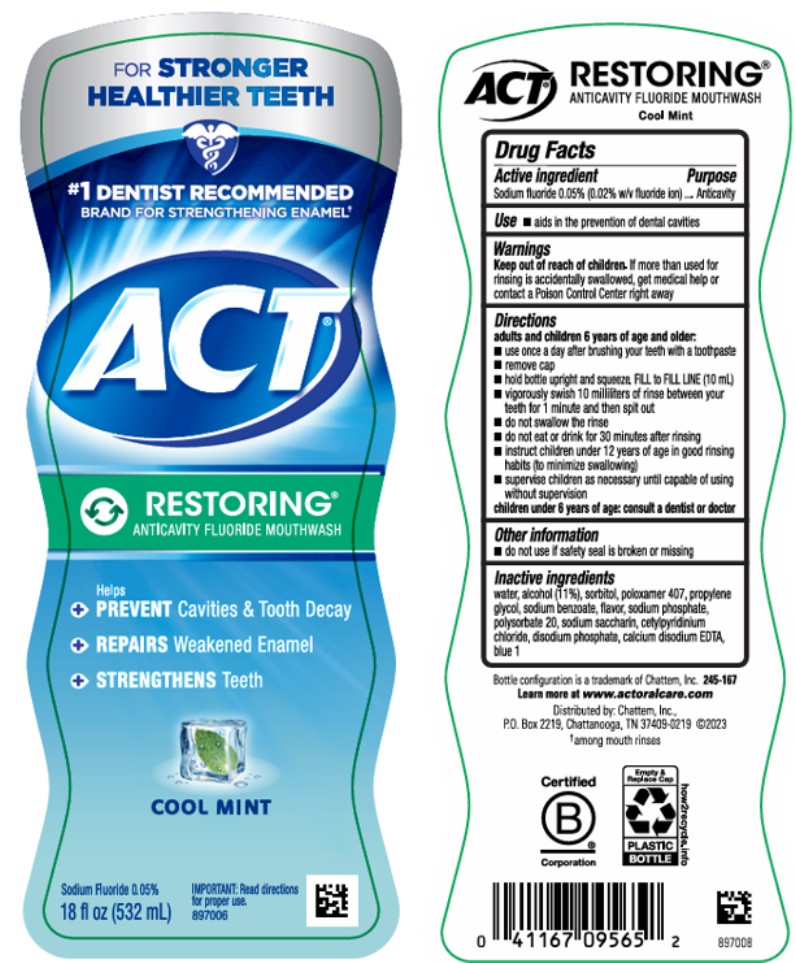 DRUG LABEL: ACT Restoring Anticavity Fluoride Cool Mint
NDC: 41167-0957 | Form: MOUTHWASH
Manufacturer: Chattem, Inc.
Category: otc | Type: HUMAN OTC DRUG LABEL
Date: 20260112

ACTIVE INGREDIENTS: SODIUM FLUORIDE 0.2 mg/1 mL
INACTIVE INGREDIENTS: WATER; ALCOHOL; SORBITOL; POLOXAMER 407; PROPYLENE GLYCOL; SODIUM BENZOATE; SODIUM PHOSPHATE; POLYSORBATE 20; SACCHARIN SODIUM; CETYLPYRIDINIUM CHLORIDE; EDETATE CALCIUM DISODIUM ANHYDROUS; FD&C BLUE NO. 1; SODIUM PHOSPHATE, DIBASIC, ANHYDROUS

ACT Restoring Anticavity Fluoride Mouthwash Cool Mint

Drug Facts

Active ingredients

Sodium fluoride 0.05% (0.02% w/v fluoride ion)

Purpose

Anticavity

Use

- aids in the prevention of dental cavities

Warnings

Keep out of reach of children

If more than used for rinsing is accidentally swallowed, get medical help or contact a Poison Control Center right away.

Directions

adults and children 6 years of age and older:

- use once a day after brushing your teeth with a toothpaste
- remove cap
- pour 10 milliliters (10 mL mark on inside of cap); do not fill above 10 mL mark
- vigorously swish 10 milliliters of rinse between your teeth for 1 minute and then spit out
- do not swallow the rinse
- do not eat or drink for 30 minutes after rinsing
- instruct children under 12 years of age in good rinsing habits (to minimize swallowing)
- supervise children as necessary until capable of using without supervision

children under 6 years of age: consult a dentist or doctor

Other information

- do not use if safety seal is broken or missing

Inactive ingredients

water, alcohol (11%), sorbitol, poloxamer 407, propylene glycol, sodium benzoate, flavor, sodium phosphate, polysorbate 20, sodium saccharin, cetylpyridinium chloride, disodium phosphate, calcium disodium EDTA, blue 1 (245-167)

www.actfluoride.com

PRINCIPAL DISPLAY PANEL

#1 DENTIST RECOMMENDED
BRAND FOR STRENGTHENING ENAMEL
ACT
RESTORING
ANTICAVITY FLUORIDE MOUTHWASH
COOL MINT
18 fl oz (532 mL)